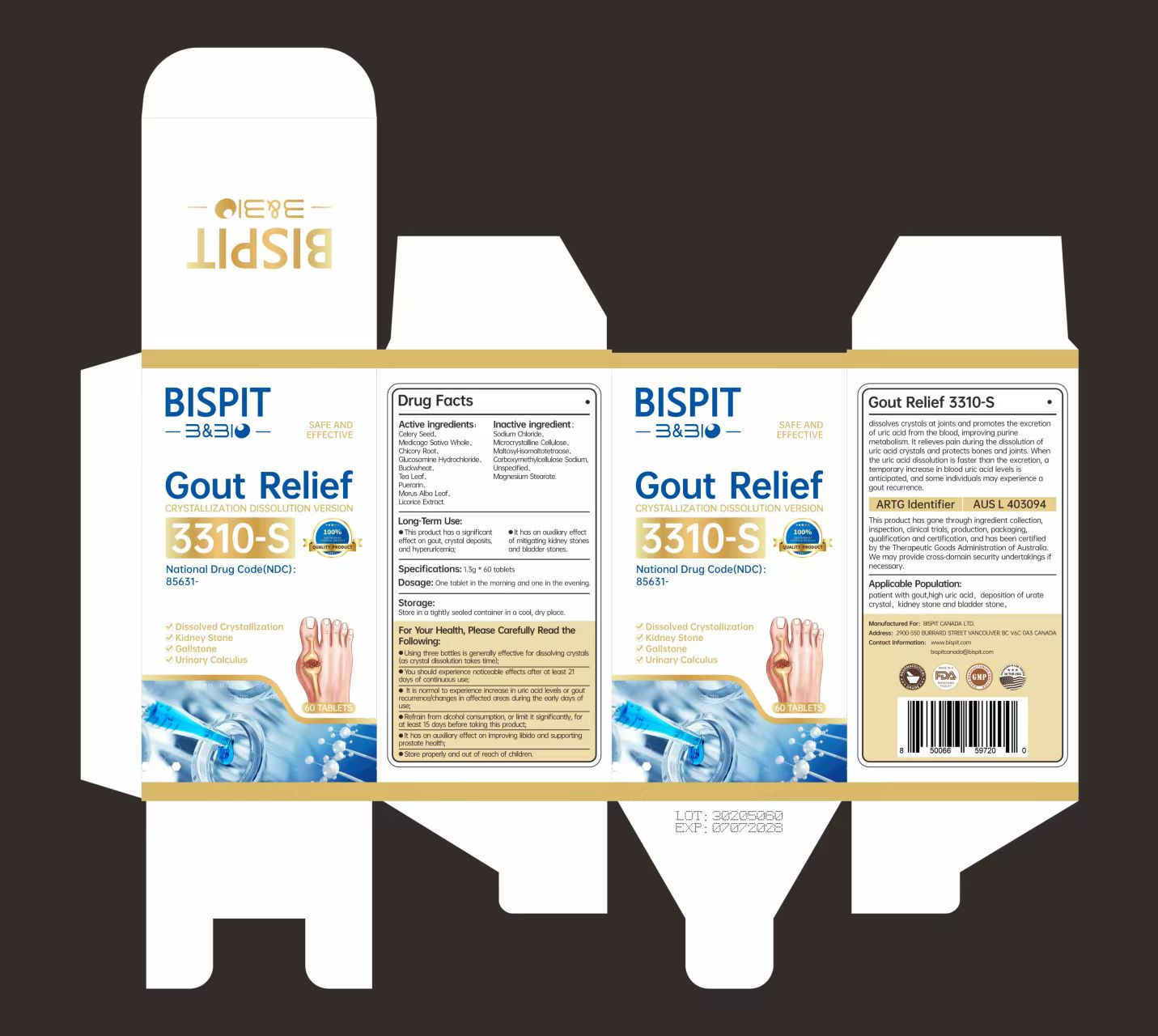 DRUG LABEL: Gout Relief 3310-S
NDC: 85631-003 | Form: CAPSULE
Manufacturer: Bispit Canada Ltd.
Category: homeopathic | Type: HUMAN OTC DRUG LABEL
Date: 20250802

ACTIVE INGREDIENTS: GLUCOSAMINE HYDROCHLORIDE 130 mg/1.3 g; MORUS ALBA LEAF 39 mg/1.3 g; LICORICE 2.6 mg/1.3 g; PUERARIN 65 mg/1.3 g; BUCKWHEAT 91 mg/1.3 g; SODIUM CHLORIDE 26 mg/1.3 g; MEDICAGO SATIVA WHOLE 260 mg/1.3 g; TEA LEAF 65 mg/1.3 g; CELERY SEED 260 mg/1.3 g; CHICORY ROOT 234 mg/1.3 g
INACTIVE INGREDIENTS: CELLULOSE GUM; CELLULOSE, MICROCRYSTALLINE; MALTOSYL-ISOMALTOTETRAOSE; MAGNESIUM STEARATE

ACTIVE INGREDIENT

CELERY SEED 1G1EAA320L 20.00%
MEDICAGO SATIVA WHOLE DJO934BRBD 20.00%
CHICORY ROOT 090CTY533N 18.00%
GLUCOSAMINE HYDROCHLORIDE 750W5330FY 10.00%
BUCKWHEAT N0Y68724R3 7.00%
TEA LEAF GH42T47V24 5.00%
PUERARIN Z9W8997416 5.00%
MORUS ALBA LEAF M8YIA49Q2P 3.00%
LICORICE 61ZBX54883 0.20%
SODIUM CHLORIDE 451W47IQ8X 2.00%

PURPOSE

This product has a significanteffect on gout, crystal deposits,and hyperuricemia;
elt has an auxiliary effectof mitigating kidney stonesand bladder stones

Keep out of reach of children

DOSAGE AND ADMINISTRATION

The product has great somatosensation after taking it atleast 21 days in the earty stage;3. Elevated uric acid or gout recurrence and site changes arenoral in the earty stage of taking this product;

INDICATIONS AND USAGE

Dissolved CrystallizationKidney StoneGallstone< Urinary Calculus

WARNINGS

For your health, please read the followingcarefully
1. The use of three vials can effectivety dissolve crystallization (ittakes time to dissolve crystallization);2. The product has great somatosensation after taking it atleast 21 days in the early stage;3. Elevated uric acid or gout recurrence and site changes arenormal in the early stage of taking this product;4. Try not to drink alcohol or drink less 15 days before takingthis product;
5. This product certainly has significant effect on gout,crystallization and hyperuricemia;

Do not use if seal is broken.

Do not eat freshness packet enclosed.

Keep out of direct sunlight, high temperature, and humidity.

Store in a cool, dry place.

INACTIVE INGREDIENT

MICROCRYSTALLINE CELLULOSE
MALTOSYL-ISOMALTOTETRAOSE
CARBOXYMETHYLCELLULOSE SODIUM, UNSPECIFIED
MAGNESIUM STEARATE